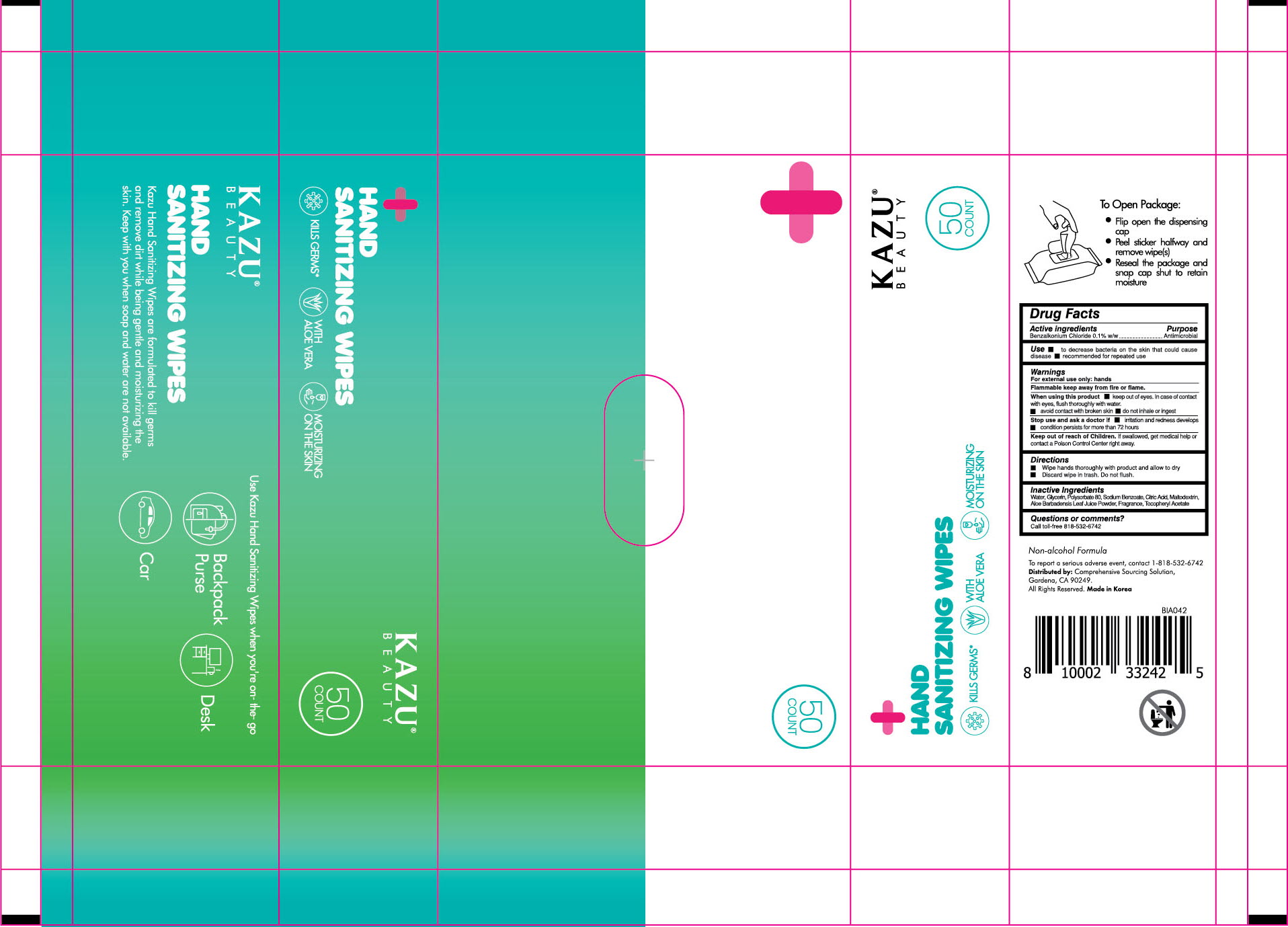 DRUG LABEL: KAZU HAND SANITIZER WIPES
NDC: 76966-0015 | Form: CLOTH
Manufacturer: N Bridge Inc.
Category: otc | Type: HUMAN OTC DRUG LABEL
Date: 20200728

ACTIVE INGREDIENTS: BENZALKONIUM CHLORIDE 0.1677 g/50 1
INACTIVE INGREDIENTS: CITRAL; GERANIOL; BENZYL SALICYLATE; FARNESOL; EDETATE DISODIUM ANHYDROUS; SODIUM BENZOATE; WATER; CITRIC ACID MONOHYDRATE; GLYCERIN; POLYSORBATE 80; .ALPHA.-TOCOPHEROL ACETATE; BENZYL BENZOATE; MALTODEXTRIN; LIMONENE, (+)-; .BETA.-CITRONELLOL, (R)-; EUGENOL; ISOEUGENOL; BENZYL ALCOHOL

ACTIVE INGREDIENT

benzalkonium chloride

INACTIVE INGREDIENT

water, glycerin, polysorbate 80, sodium benzoate, benzalkonium chloride, citric acid, maltodextrin, aloe barbadensis leaf juice powder, limonene, tocopheryl acetate, linalool, citral, citronellol, geraniol, benzyl benzoate, benzyl salicylate, farnesol, eugenol, isoeugenol, benzyl alcohol, fragrance

PURPOSE

Antiseptic

keep out of reach of the children

INDICATIONS AND USAGE

Wipe hands thoroughly with product and allow to dry.

Discard wipe in trash. Do not flush.

WARNINGS

For external use only. Flammable. Keep away from heat or flame.

When using this product keep out of eyes. in case of contact with eyes, flush thoroughly with water.

avoid contact with broken skin.

do not inhale or ingest.

Stop use and ask a doctor if irritation and redness develop. condition persists for more than 72 hours.

Keep out of reach of children. If swallowed, get medical help or contact a Poison Control Center right away.

DOSAGE AND ADMINISTRATION

for external use only